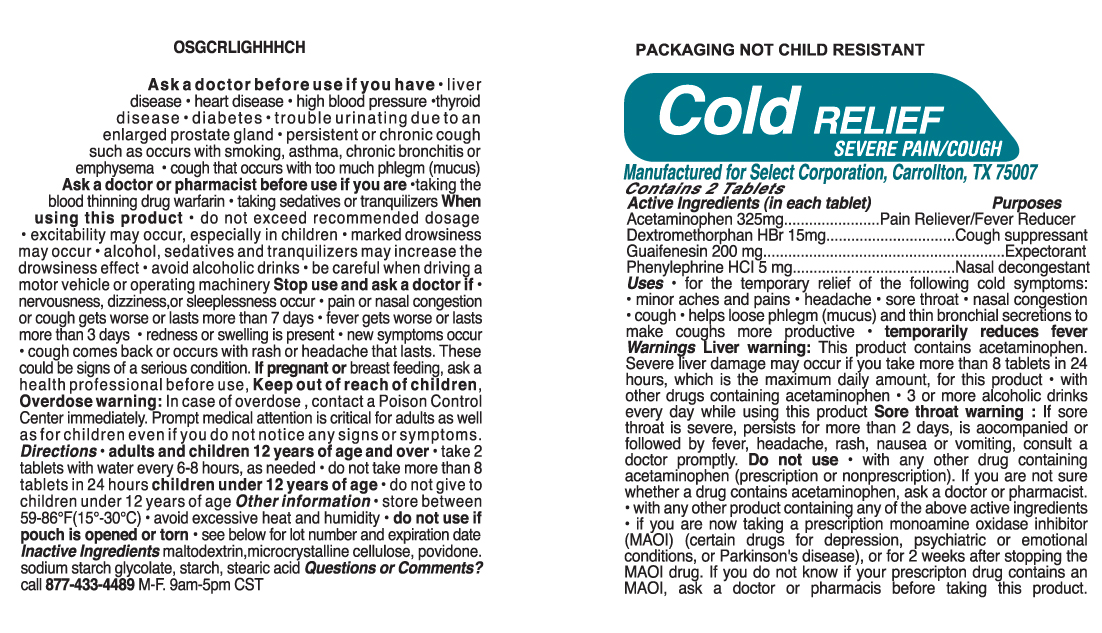 DRUG LABEL: Cold Relief Severe Pain Cough
                
NDC: 52904-456 | Form: TABLET
Manufacturer: Select Corporation
Category: otc | Type: HUMAN OTC DRUG LABEL
Date: 20121015

ACTIVE INGREDIENTS: ACETAMINOPHEN 325 mg/1 1; PHENYLEPHRINE HYDROCHLORIDE 5 mg/1 1; GUAIFENESIN 200 mg/1 1; DEXTROMETHORPHAN HYDROBROMIDE 15 mg/1 1
INACTIVE INGREDIENTS: MALTODEXTRIN; STARCH, CORN; STEARIC ACID; SODIUM STARCH GLYCOLATE TYPE A POTATO; POVIDONE K29/32; CELLULOSE, MICROCRYSTALLINE

Drug Facts

Active Ingredients

Acetaminophen 325 mg.Guaifenesin 200 mg Phenylephrine HCl 5 mg

PURPOSE

Pain Reliever, Fever Reducer, Expectorant, Nasal Decongestant, Cough Suppressant

DOSAGE AND ADMINISTRATION

Directions: adults and children 12 years of age and over • take 2 tablets with water every 6-8 hours, as needed • do not take more than 8 tablets in 24 hours children under 12 years of age • do not give to children under 12 years of age

INDICATIONS AND USAGE

Uses: or the temporary relief of the following cold symptoms: • minor aches and pains • headache • sore throat • nasal congestion • cough • helps loose phlegm (mucus) and thin bronchial secretions to make coughs more productive • temporarily reduces fever

WARNINGS

Warnings: Liver warning: This product contains acetaminophen. Severe liver damage may occur if you take more than 8 tablets in 24 hours, which is the maximum daily amount, for this product • with other drugs containing acetaminophen • 3 or more alcoholic drinks every day while using this product Sore throat warning : If sore throat is severe, persists for more than 2 days, is accompanied or followed by fever, headache, rash, nausea or vomiting, consult a doctor promptly. Do not use • with any other drug containing acetaminophen (prescription or nonprescription). If you are not sure whether a drug contains acetaminophen, ask a doctor or pharmacist. • with any other product containing any of the above active ingredients • if you are now taking a prescription monoamine oxidase inhibitor (MAOI) (certain drugs for depression, psychiatric or emotional conditions, or Parkinson's disease), or for 2 weeks after stopping the MAOI drug. If you do not know if your prescription drug contains an MAOI, ask a doctor or pharmacist before taking this product. Ask a doctor before use if you have • liver disease • heart disease • high blood pressure •thyroid disease • diabetes • trouble urinating due to an enlarged prostate gland • persistent or chronic cough such as occurs with smoking, asthma, chronic bronchitis or emphysema • cough that occurs with too much phlegm (mucus) Ask a doctor or pharmacist before use if you are •taking the blood thinning drug warfarin • taking sedatives or tranquilizers When
using this product • do not exceed recommended dosage • excitability may occur, especially in children • marked drowsiness may occur • alcohol, sedatives and tranquilizers may increase the drowsiness effect • avoid alcoholic drinks • be careful when driving a motor vehicle or operating machinery Stop use and ask a doctor if • nervousness, dizziness,or sleeplessness occur • pain or nasal congestion or cough gets worse or lasts more than 7 days • fever gets worse or lasts more than 3 days • redness or swelling is present • new symptoms occur • cough comes back or occurs with rash or headache that lasts. These could be signs of a serious condition.

PREGNANCY OR BREAST FEEDING

If pregnant or breast-feeding baby, ask a health professional
before use.

KEEP OUT OF REACH OF CHILDREN.

Inactive ingredients:
Maltodextrin, Microcrystalline Cellulose, Povidone, Sodium Starch Glycolate, Starch, Stearic Acid

PACKAGE LABEL

MM1